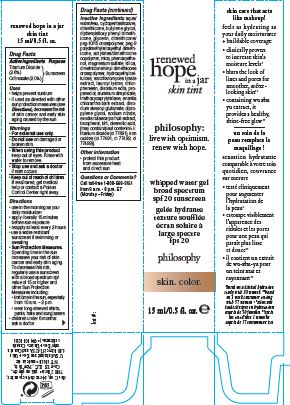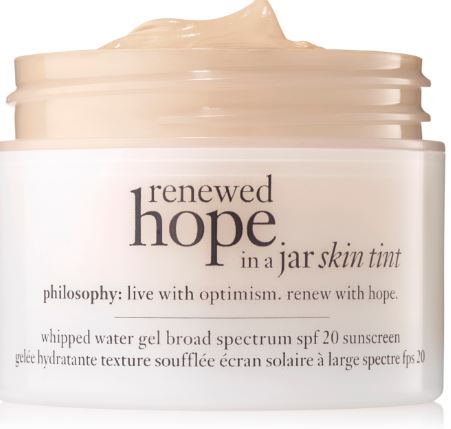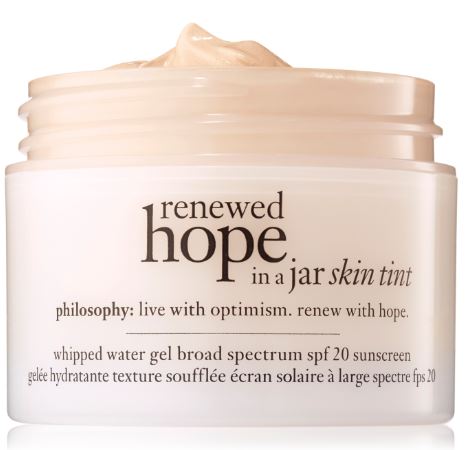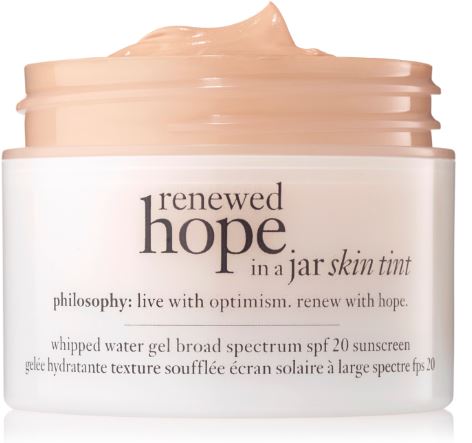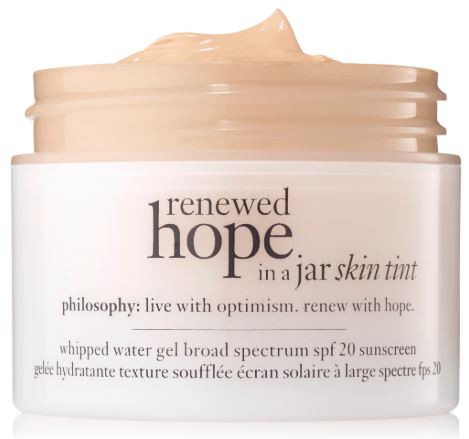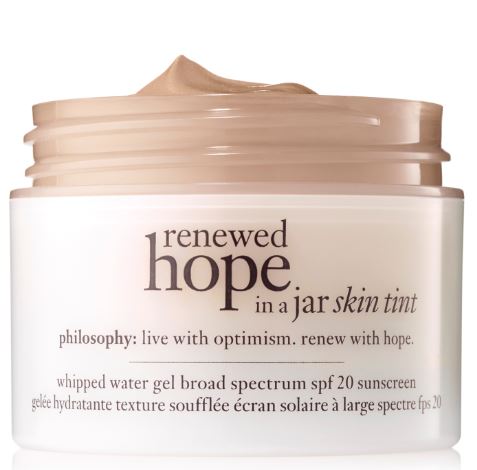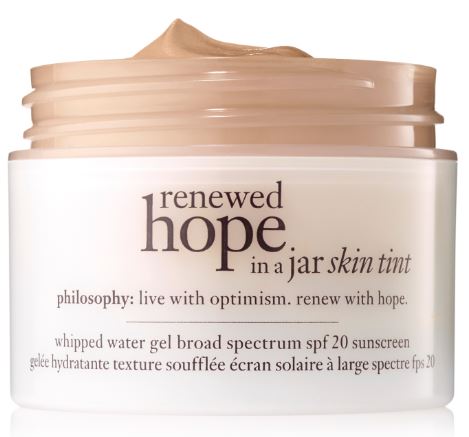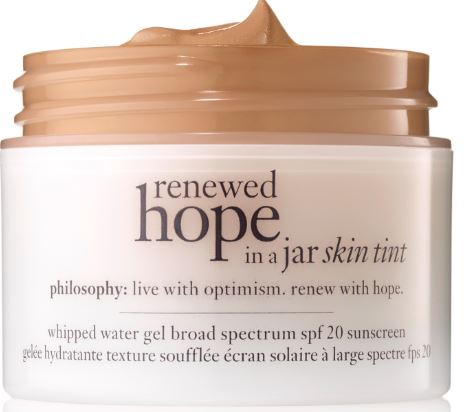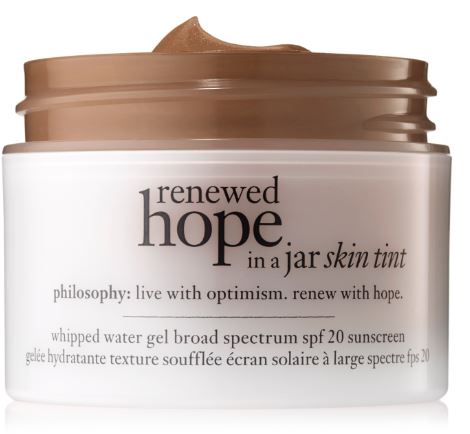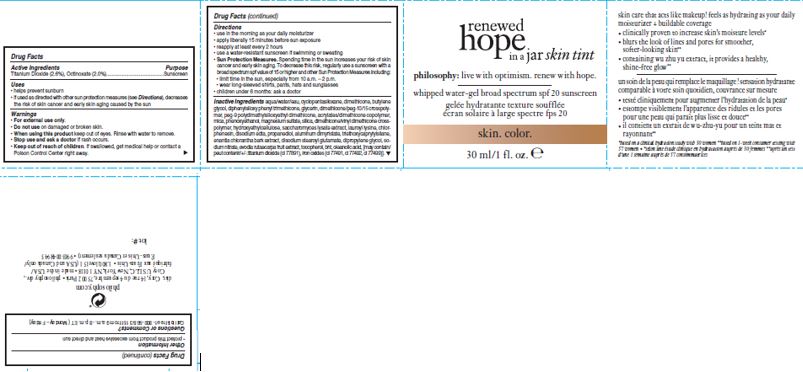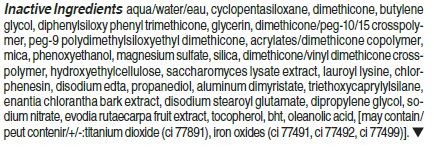 DRUG LABEL: renewed hope in a jar skin tint spf 20
NDC: 50184-1063 | Form: LIQUID
Manufacturer: PHILOSOPHY, INC.
Category: otc | Type: HUMAN OTC DRUG LABEL
Date: 20200211

ACTIVE INGREDIENTS: TITANIUM DIOXIDE 2.6 g/100 mL; OCTINOXATE 2 g/100 mL
INACTIVE INGREDIENTS: WATER; MICA; DIMETHICONE; PHENOXYETHANOL; MAGNESIUM SULFATE, UNSPECIFIED; ALUMINUM DIMYRISTATE; SODIUM NITRATE

renewed hope in a jar skin tint spf 20

Active Ingredients

Titanium Dioxide (2.6%), Octinoxate (2.0%)

Purpose

Sunscreen

Uses

helps prevent sunburn

if used as directed with other sun protection measures (see Directions), decreases the risk of skin cancer and early skin aging caused by the sun.

Warnings

For external use only.

Do not use

on damaged or broken skin.

When using this product

keep out of eyes. Rinse with water to remove.

Stop use and ask a doctor

if rash occurs.

Keep out of reach of children.

If swallowed, get medical help or contact a Poison Control Center right away.

Directions

use in the morning as your daily moisturizer

apply liberally 15 minutes before sun exposure

reapply at least every 2 hours

use a water resistant sunscreen if swimming or sweating

Sun Protection Measures. Spending time in the sun increases your risk of skin cancer and early skin aging. To decrease this risk, regularly use a sunscreen with a Broad Spectrum SPF value of 15 or higher and other sun protection measures including: [bullet] limit time in the sun, especially from 10 a.m.-2 p.m. [bullet] wear long-sleeved shirts, pants, hats, and sunglasses.
children under 6 months of age: ask a doctor

Other Information

protect this product in this container from excessive heat and direct sun

Questions or Comments?

Call toll-free 1-800-568-3151 from 9 a.m.-8 p.m. ET (Monday-Friday)

PACKAGE LABEL

renewed

hope

in a jar skin tint

philosophy: live with optimism. renew with hope.

whipped water-gel broad spectrum spf 20 sunscreen

skin. color.